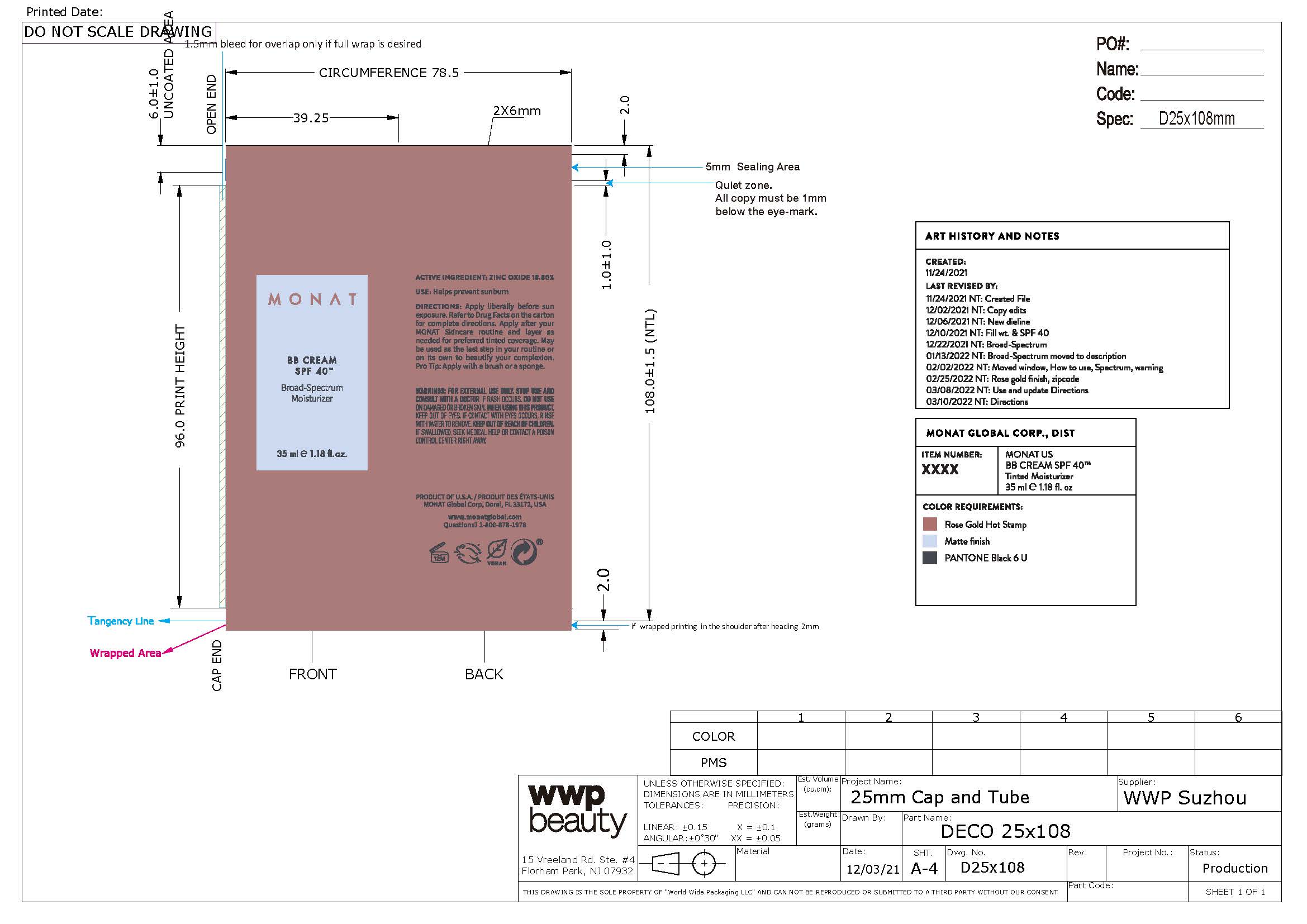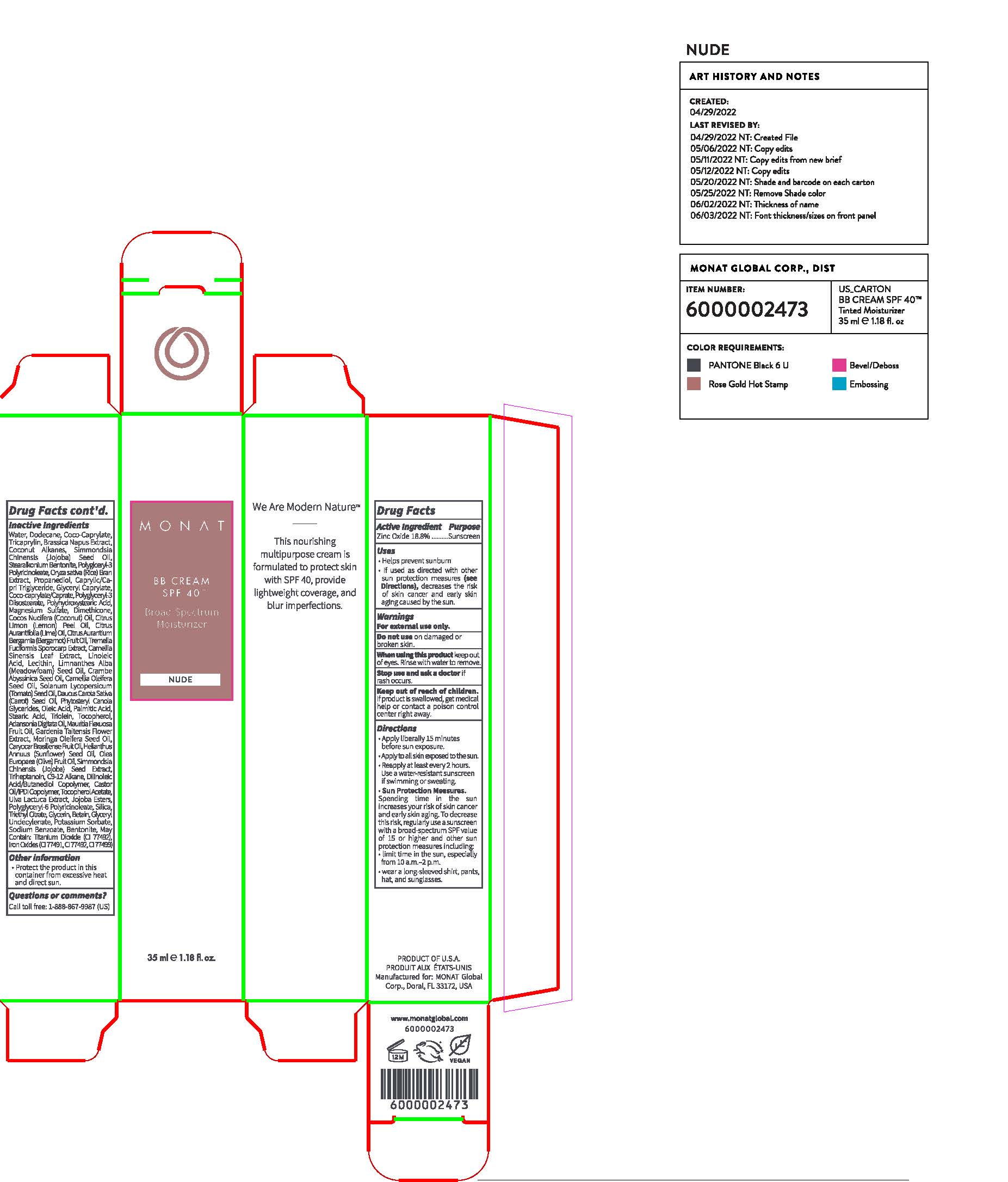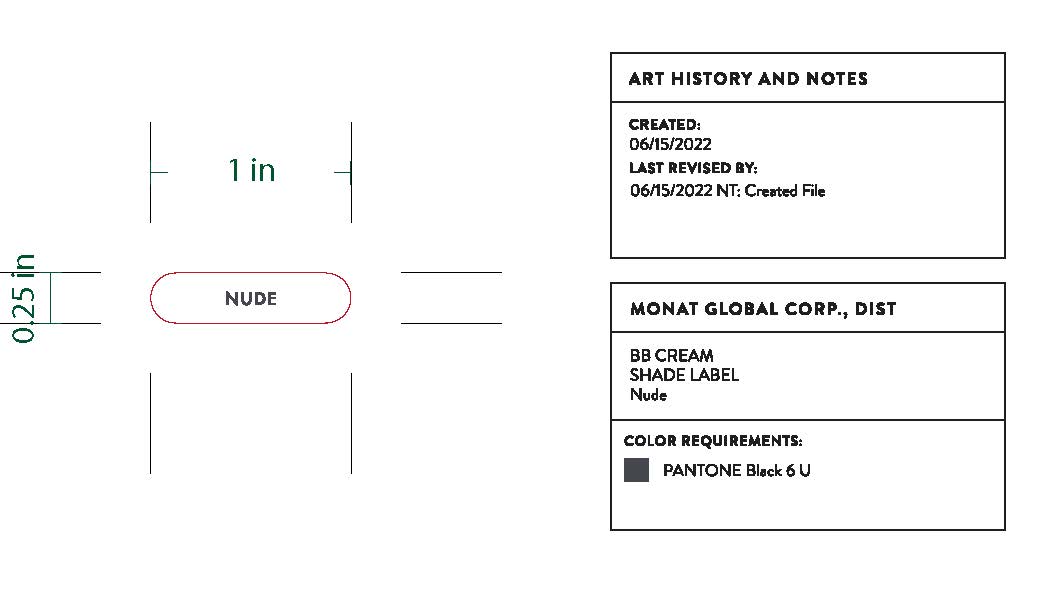 DRUG LABEL: Cream
NDC: 61354-113 | Form: CREAM
Manufacturer: Oxygen Development LLC
Category: otc | Type: HUMAN OTC DRUG LABEL
Date: 20230707

ACTIVE INGREDIENTS: ZINC OXIDE 18.8 mg/100 mg
INACTIVE INGREDIENTS: TRICAPRYLIN 7 mg/100 mg; JOJOBA OIL 2.55 mg/100 mg; POLYGLYCERYL-3 PENTARICINOLEATE 2.04 mg/100 mg; RICE BRAN 2 mg/100 mg; COCO-CAPRYLATE 1.99 mg/100 mg; POLYGLYCERYL-3 DIISOSTEARATE 1.04 mg/100 mg; DIMETHICONE 1 mg/100 mg; TRIHEPTANOIN 0.91 mg/100 mg; WATER 28.27 mg/100 mg; STEARALKONIUM ION 2.6 mg/100 mg; BENTONITE 0.93 mg/100 mg; DODECANE 11.96 mg/100 mg; BRASSICA NAPUS WHOLE 3.5 mg/100 mg; GLYCERYL CAPRYLATE 1.33 mg/100 mg; MAGNESIUM SULFATE, UNSPECIFIED 1 mg/100 mg; PROPANEDIOL 2 mg/100 mg; POLYHYDROXYSTEARIC ACID STEARATE 1.2 mg/100 mg; MEDIUM-CHAIN TRIGLYCERIDES 1.5 mg/100 mg; COCO-CAPRYLATE/CAPRATE 1.32 mg/100 mg; TRIETHYL CITRATE 0.52 mg/100 mg; TITANIUM DIOXIDE 2.39 mg/100 mg; FERRIC OXIDE RED 1.03 mg/100 mg

MONAT BB CREAM SPF 40 Broad-Spectrum Moisturizer

Active ingredient

Zinc Oxide 18.8%

Purpose

Sunscreen

Uses

Helps prevent sunburn

If used as directed with other sun protection measures (see Directions), decreases the risk of skin cancer and early skin aging caused by the sun

Warnings

For external use only

Do not use on damaged or broken skin

When using this product

Keep out of eyes. Rinse with water to remove.

Stop use and ask a doctor if rash occurs

Keep out of reach of children

If product is swallowed, get medical help or contact a poison control center right away

Directions

Apply liberally 15 minutes before sun exposure.

Apply to all skin exposed to the sun.

Reapply at least every 2 hours. Use a water-resistant sunscreen if swimming or sweating.

Sun protection measures.

Spending time in the sun increases your risk of skin cancer and early skin aging. To decrease the risk, regularly use a sunscreen with a board-spectrum SPF value of 15 or higher and other sun protection measures including:

limit time in the sun, especially from 10 a.m. - 2 p.m.

wear a long-sleeved shirt, pants, hat, and sunglasses

Inactive Ingredient

Water, Dodecane, Coco-Caprylate, Tricaprylin, Brassica Napus Extract, Coconut Alkanes, Simmondsia Chinensis (Jojoba) Seed Oil, Stearalkonium Bentonite, Polyglyceryl-3 Polyricinoleate, Oryza Sativa (Rice) Bran Extract, Propanediol, Caprylic/Capric Triglyceride, Glyceryl Caprylate, Coco-Caprylate/Caprate, Polyglyceryl-3 Diisostearate, Polyhydroxystearic Acid, Magnesium Sulfate, Dimethicone, Cocos Nucifera (Coconut) Oil, Citrus Limon (Lemon) Peel Oil, Citrus Aurantofolia (Lime) Oil, Citrus Aurantium Bergamia (Bergamot)Fruit Oil, Tremella Fucformis Sporocarp Extract, Camelia Sinensis Leaf Extract, Linoleic Acid, Lecithin, Limnanther Alba (Meadowfoam (Speed Oil, Crambe Abyssinica Seed Oil, Camelia Oleifera Seed Oil, Solanum Lycopersicum (Tomato) Seed Oil, Daucus Carota Sativa (Carrot) Seed Oil, Phytosteryl Canola Glycerides, Oleic Acid, Palmitic Acid, Stearic Acid, Triolein, Tocopherol, Adansonia Digitata Oil, Maurita Flexuosa Fruit Oil, Gardenia Taitensis Flowe Extract, Moringa Oleifera Seed Oil, Caryocar Brasiliense Fruit Oil, Helianthus Annuus (Sunflower) Seed Oil, Olea Europea (Olive) Fruit Oil, Simmondsia Chinensis (Jojoba) Seed Extract, Triheptanoin, C9-12 Alkane, Dilinoleic Acid/Butanediol Copolymer, Castor Oil/IPDI Copolymer, Tocopherol Acetate, Ulva Lactuca Extract, Jojoba Esters, Polyglyceryl-6 Polyricinoleate, Silica, Triethyl Citrate, Glycerin, Betain, Glyceryl Undecylenate, Potassium Sorbate, Sodium Benzoate, Bentonite, May Contain: Titanium Dioxide (CI 77492), Iron Oxides (CI 77491, CI 77492, CI 77499)

Other Information

Protect the product in this container from excessive heat and direct sun